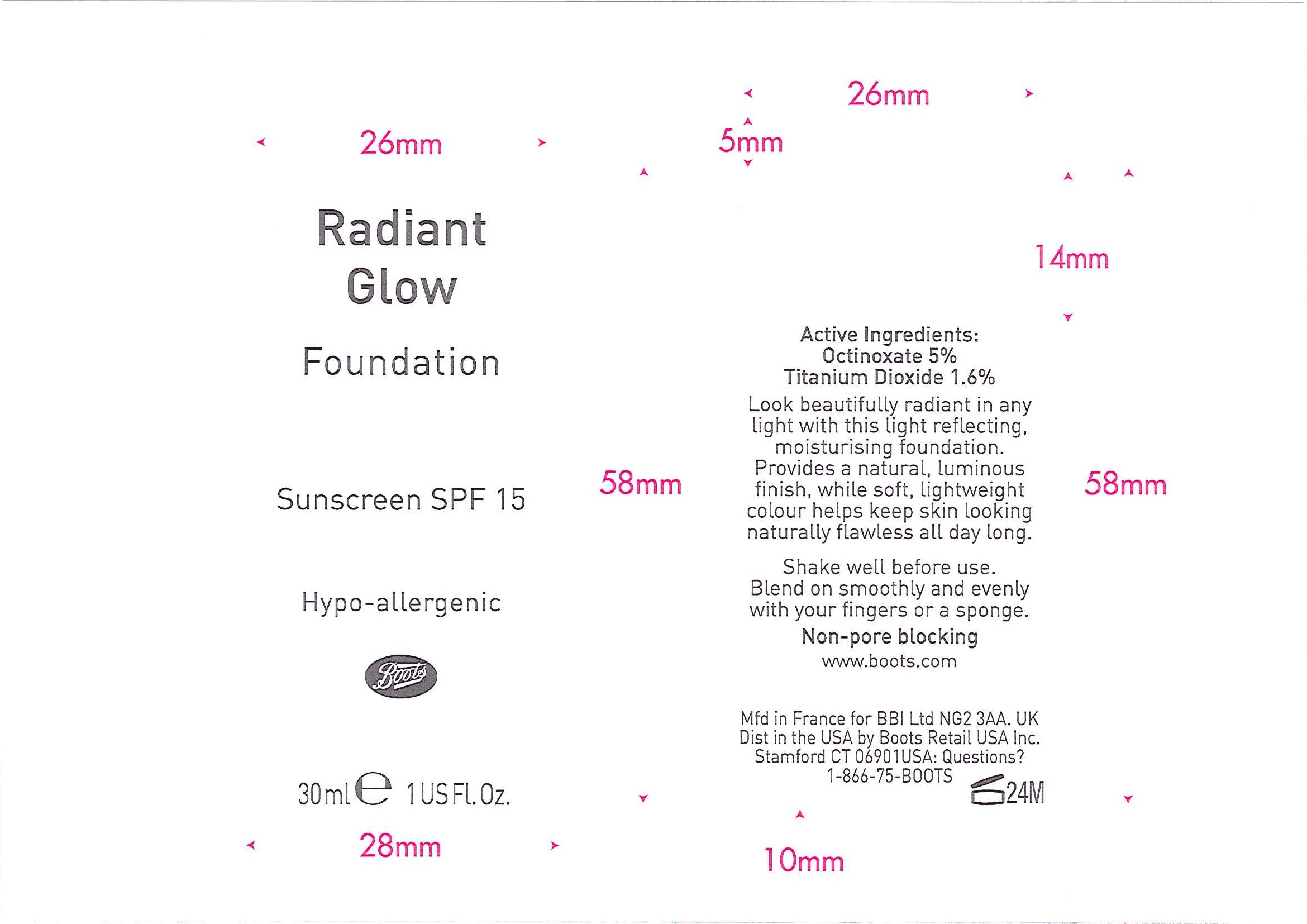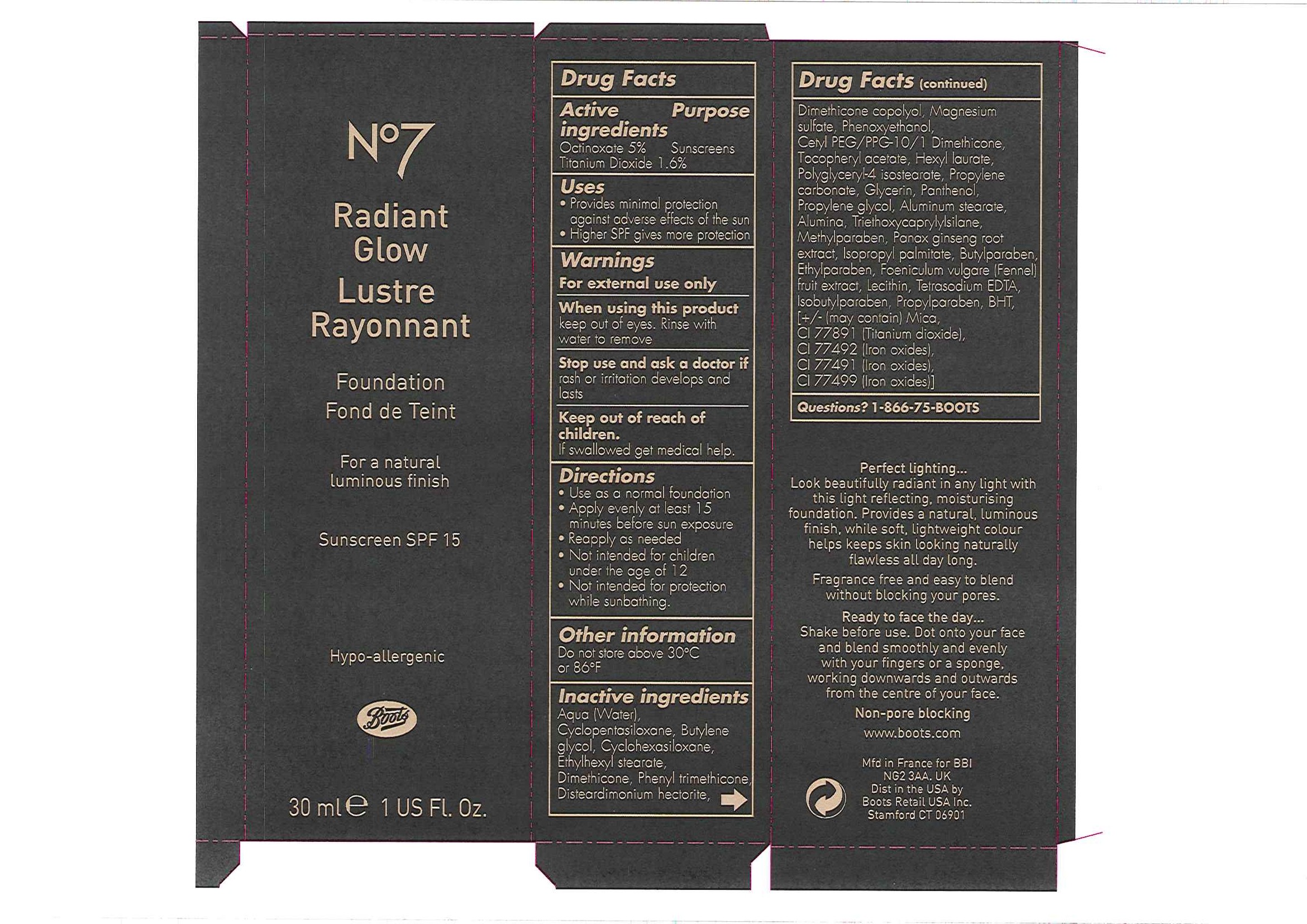 DRUG LABEL: No7 Radiant Glow Foundation Sunscreen SPF 15  Cocoa
NDC: 68472-098 | Form: EMULSION
Manufacturer: Boots Retail USA Inc
Category: otc | Type: HUMAN OTC DRUG LABEL
Date: 20100324

ACTIVE INGREDIENTS: OCTINOXATE 1.5 mL/30 mL; TITANIUM DIOXIDE 0.48 mL/30 mL
INACTIVE INGREDIENTS: WATER; CYCLOMETHICONE 5; BUTYLENE GLYCOL; CYCLOMETHICONE 6; DIMETHICONE; PHENYL TRIMETHICONE; MAGNESIUM SULFATE; PHENOXYETHANOL; .ALPHA.-TOCOPHEROL ACETATE, DL-; HEXYL LAURATE; POLYGLYCERYL-4 ISOSTEARATE; PROPYLENE CARBONATE; GLYCERIN; PANTHENOL; PROPYLENE GLYCOL; ALUMINUM STEARATE; ALUMINUM OXIDE; OCTYLTRIETHOXYSILANE; METHYLPARABEN; ASIAN GINSENG; ISOPROPYL PALMITATE; BUTYLPARABEN; ETHYLPARABEN; FENNEL OIL; LECITHIN, SOYBEAN; EDETATE SODIUM; ISOBUTYLPARABEN; PROPYLPARABEN; BUTYLATED HYDROXYTOLUENE; FERRIC OXIDE YELLOW; FERRIC OXIDE RED; FERROSOFERRIC OXIDE

Carton and bottle labelling

Active Ingredients Purpose

Octinoxate 5% Sunscreens

Titanium Dioxide 1.6%

Uses

- Provides minimal protection against adverse effects of the sun
- Higher SPF gives more protection

Warnings

For external use only

When using this product

Keep out of eyes. Rinse with water to remove.

Stop use and ask a doctor if rash or irritation develops and lasts

Keep out of reach of children.

If swallowed get medical help.

Directions

- Use as a normal foundation
- Apply evenly at least 15 minutes before sun exposure
- Reapply as needed
- Not intended for children under the age of 12
- Not intended for protection while sunbathing

Other information

Do not store above 30oC or 86oF

Inactive ingredients

Aqua (Water), Cyclopentasiloxane, Butylene glycol, Cyclohexasiloxane, Ethylhexyl stearate, Dimethicone, Phenyl trimethicone, Disteardimonium hectorite, Dimethicone copolyol, Magnesium sulfate, Phenoxyethanol, Cetyl PEG/PPG-10/1 Dimethicone, Tocopheryl acetate, Hexyl laurate, Polyglyceryl-4 isostearate, Propylene carbonate, Glycerin, Panthenol, Propylene glycol, Aluminum stearate, Alumina, Triethoxycaprylylsilane, Methylparaben, Panax ginseng root extract, Isopropyl palmitate, Butylparaben, Ethylparaben, Foeniculum vulgare (Fennel) fruit extract, Lecithin, Tetrasodium EDTA, Isobutylparaben, Propylparaben, BHT, [+/- (may contain) Mica, CI 77891 (Titanium dioxide), CI 77492 (Iron oxides), CI 77491 (Iron oxides), CI 77499 (Iron oxides).

Questions? 1-866-75-BOOTS

DESCRIPTION

Perfect lighting...
Look beautifully radiant in any light with this light reflecting, moisturising foundation. Provides a natural, luminous finish, while soft, lightweight colour helps keep skin looking naturally flawless all day long.
Fragrance free and easy to blend without blocking your pores.
Ready to face the day...
Shake before use. Dot onto your face and blend smoothly and evenly with your fingers or a sponge, working downwards and outwards from the centre of your face.
Non-pore blocking.

PATIENT COUNSELING INFORMATION

www.boots.com

Mfd in France for BBI NG2 3AA. UK

Dist in the USA by Boots Retail USA Inc Stamford CT 06901

ACTIVE INGREDIENT

Bottle label
Active Ingredients:
Octinoxate 5%
Titanium Dioxide 1.6%

DESCRIPTION

Look beautifully radiant in any light with this light reflecting, moisturising foundation. Provides a natural, luminous finish, while soft, lightweight colour helps keep skin looking naturally flawless all day long.
Shake well before use. Blend on smoothly and evenly with your fingers or a sponge.

Non-pore blocking.

PATIENT COUNSELING INFORMATION

www.boots.com

Mfd in France for BBI Ltd NG2 3AA. UK

Dist in the USA by Boots Retail USA Inc. Stamford CT 06901

USA: Questions? 1-866-75-BOOTS

PACKAGE LABEL

No7

Radiant Glow

Lustre Rayonnant

Foundation

Fond de Teint

For a natural luminous finish

Sunscreen SPF 15

Hypo-allergenic
Boots
30ml e 1 US Fl. Oz
Radiant Glow Fdn carton.jpg

Bottle label

Radiant Glow

Foundation

Sunscreen SPF 15

Hypo-allergenic

Boots

30ml e 1 US Fl. Oz

Radiant Glow Fdn bottle labels.jpg